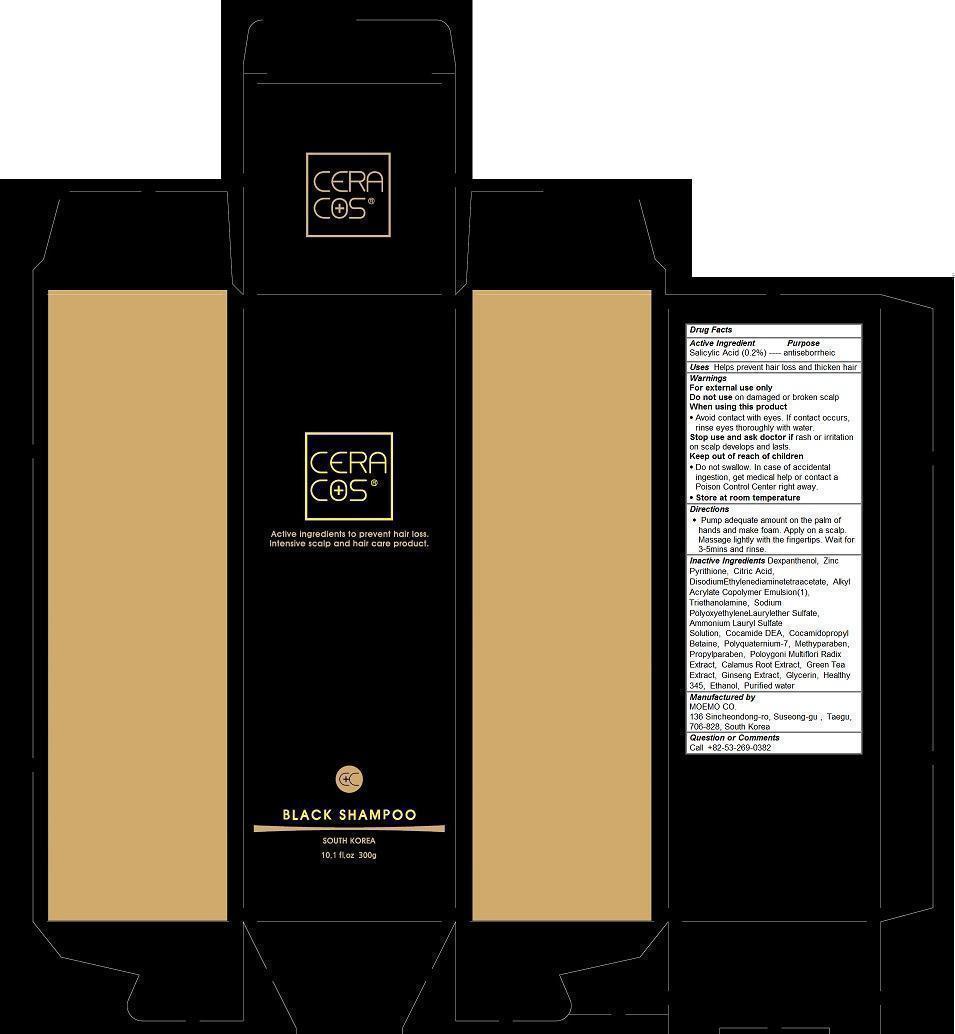 DRUG LABEL: MOEMO CERACOS Black
NDC: 69658-101 | Form: SHAMPOO
Manufacturer: MOEMO CO.
Category: otc | Type: HUMAN OTC DRUG LABEL
Date: 20150317

ACTIVE INGREDIENTS: Salicylic Acid 0.2 1/300 g
INACTIVE INGREDIENTS: Dexpanthenol; PYRITHIONE ZINC; CITRIC ACID MONOHYDRATE; EDETATE DISODIUM; TROLAMINE; SODIUM LAURETH-2 SULFATE; AMMONIUM LAURYL SULFATE; COCO DIETHANOLAMIDE; COCAMIDOPROPYL BETAINE; POLYQUATERNIUM-7 (70/30 ACRYLAMIDE/DADMAC; 1600000 MW); METHYLPARABEN; PROPYLPARABEN; JATEORHIZA CALUMBA ROOT; GREEN TEA LEAF; ASIAN GINSENG; GLYCERIN; ALCOHOL; water

MOEMO CERACOS Black Shampoo